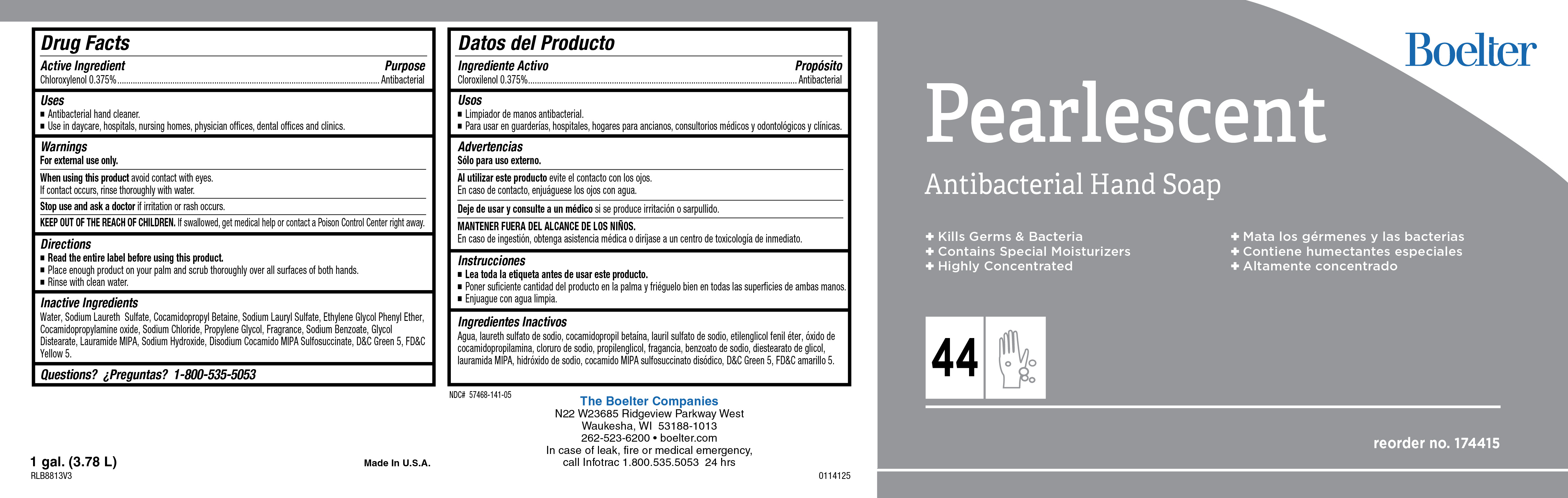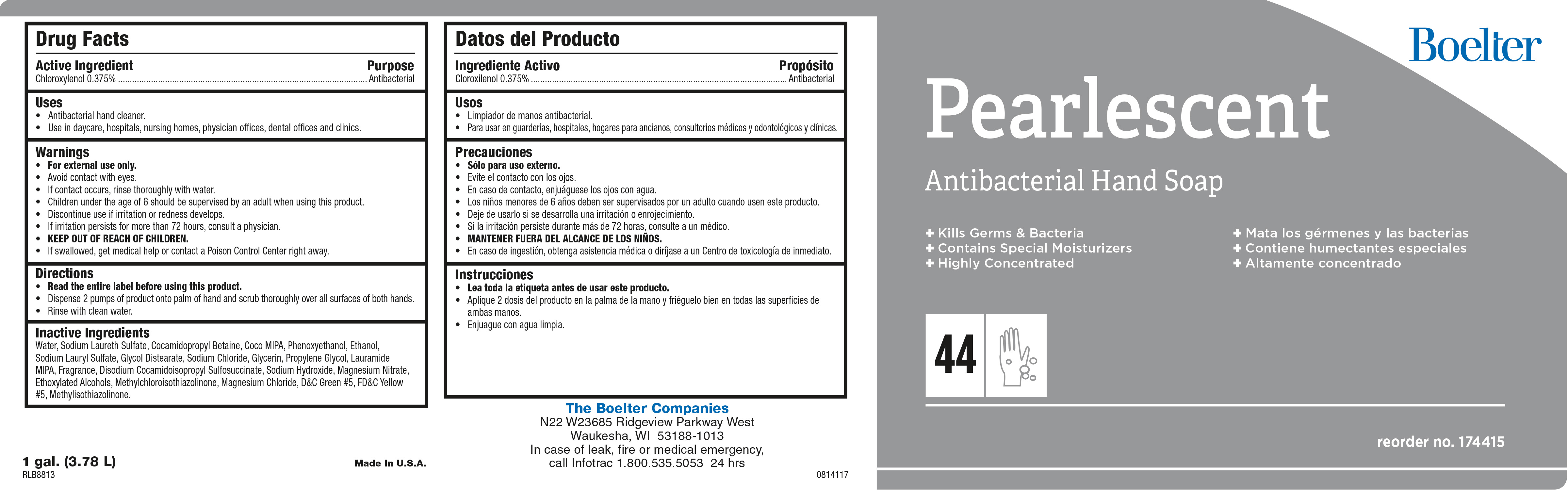 DRUG LABEL: Pearlescent
NDC: 57468-141 | Form: SOAP
Manufacturer: Boelter Companies Inc.
Category: otc | Type: HUMAN OTC DRUG LABEL
Date: 20241226

ACTIVE INGREDIENTS: CHLOROXYLENOL 3.75 mg/1 mL
INACTIVE INGREDIENTS: CALCIUM SILICATE; ETHYLENE BRASSYLATE; BENZYL SALICYLATE; DIHYDROMYRCENOL; COCAMIDOPROPYLAMINE OXIDE; PHENYLETHYL ALCOHOL; TRIBASIC CALCIUM PHOSPHATE; .ALPHA.-AMYLCINNAMALDEHYDE; WATER; COCAMIDOPROPYL BETAINE; PHENOXYETHANOL; PROPYLENE GLYCOL; D&C GREEN NO. 5; FD&C YELLOW NO. 5; SODIUM ALUMINIUM SILICATE; SODIUM LAURYL SULFATE; SODIUM CARBONATE; ETHYLENE OXIDE; LINALOOL, (+/-)-; GLYCOL DISTEARATE; SODIUM HYDROXIDE; 1-(2,3,8,8-TETRAMETHYL-1,2,3,4,5,6,7,8-OCTAHYDRONAPHTHALEN-2-YL)ETHANONE; LAURIC ISOPROPANOLAMIDE; 2-TERT-BUTYLCYCLOHEXYL ACETATE; 4-ACETOXY-3-PENTYLTETRAHYDROPYRAN; HEXAHYDRO-4,7-METHANOINDEN-6-YL PROPIONATE; .ALPHA.-HEXYLCINNAMALDEHYDE; SODIUM CHLORIDE; 2-ISOBUTYL-4-METHYLTETRAHYDROPYRAN-4-OL; SODIUM LAURETH SULFATE; 2,6-DIMETHYL-5-HEPTENAL; 3-(3,4-METHYLENEDIOXYPHENYL)-2-METHYLPROPANAL; SODIUM BENZOATE; VERDYL ACETATE; .GAMMA.-UNDECALACTONE; BENZYL ACETATE; HEXYL SALICYLATE; .BETA.-CITRONELLOL, (+/-)-

Pearlescent

Pearlescent

Active Ingredient

Chloroxylenol 0.375%

Pearlescent

Uses

- Antibacterial hand cleaner.
- Use in daycare, hospitals, nursing homes, physicians offices, dental offices and clinics

Pearlescent

Warnings

- For external use only.
- Avoid contact with eyes.
- Children under the age of 6 should be supervised by an adult when using this product.
- Discontinue use is irritation or redness develops.
- If irritation persists for more than 72 hours, consult a physician.
- KEEP OUT OF REACH OF CHILDREN.

Pearlescent

Directions

- Read the entire label before using this product.
- Dispense 1-2 pumps of product onto wet palm.
- Lather and rinse hands with clean water

Pearlescent

Inactive Ingredients

Water, Sodium Lauryl lSulfate, Cocamide DEA, Cocamidopropyl betadine, Phenoxyethanol, Sodium Laureth Sulfate, Propylene Glycol, Fragrance, DMDM Hydantoin, Glycol Stearate, Laurimide DEA, Glycerine, Tocopheryl Acetate, D&C Green #5, FD&C Yellow #5.

Pearlescent

Purpose

Antibacterial

Pearlescent

KEEP OUT OF REACH OF CHILDREN